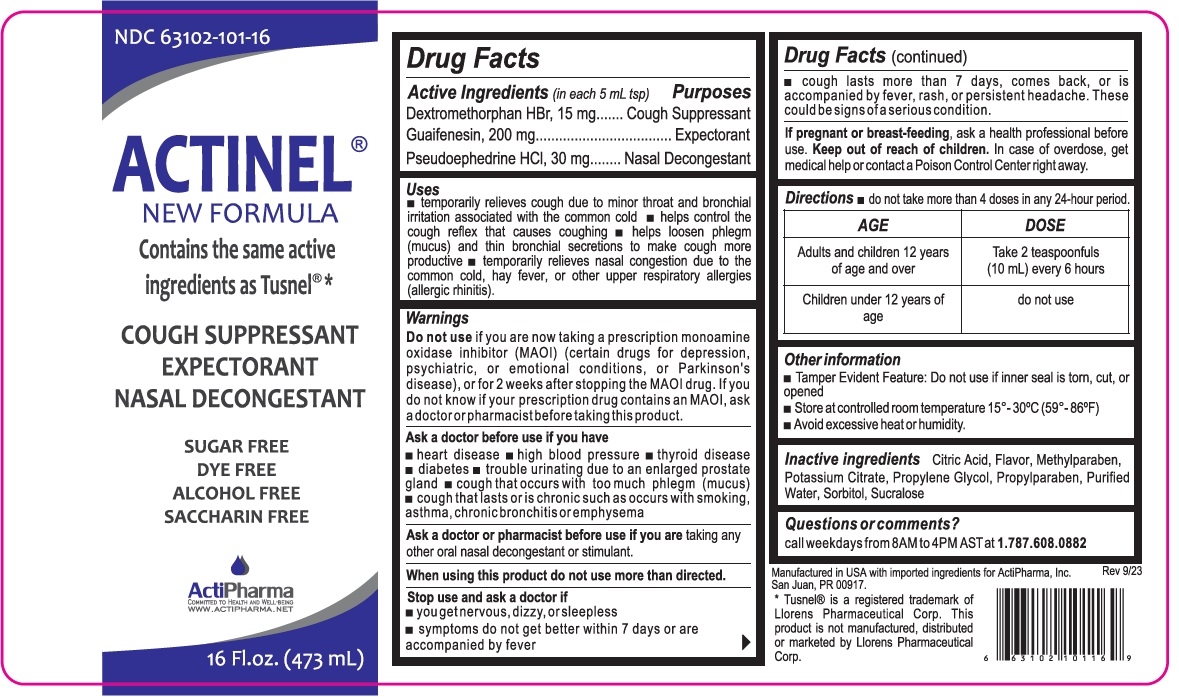 DRUG LABEL: ACTINEL
NDC: 63102-101 | Form: SOLUTION
Manufacturer: ACTIPHARMA, LLC
Category: otc | Type: HUMAN OTC DRUG LABEL
Date: 20250708

ACTIVE INGREDIENTS: DEXTROMETHORPHAN HYDROBROMIDE 15 mg/5 mL; GUAIFENESIN 200 mg/5 mL; PSEUDOEPHEDRINE HYDROCHLORIDE 30 mg/5 mL
INACTIVE INGREDIENTS: CITRIC ACID MONOHYDRATE; METHYLPARABEN; POTASSIUM CITRATE; PROPYLENE GLYCOL; PROPYLPARABEN; WATER; SORBITOL; SUCRALOSE

ACTINEL®

Active Ingredients (in each 5 mL tsp)

Dextromethorphan HBr, 15 mg
Guaifenesin, 200 mg
Pseudoephedrine HCl, 30 mg

Purposes

Cough Suppressant
Expectorant
Nasal Decongestant

Uses

• temporarily relieves cough due to minor throat and bronchial irritation associated with the common cold • helps control the cough reflex that causes coughing • helps loosen phlegm (mucus) and thin bronchial secretions to make cough more productive • temporarily relieves nasal congestion due to the common cold, hay fever, or other upper respiratory allergies (allergic rhinitis).

Warnings

Do not use if you are now taking a prescription monoamine oxidase inhibitor (MAOI) (certain drugs for depression, psychiatric, or emotional conditions, or Parkinson’s disease), or for 2 weeks after stopping the MAOI drug. If you do not know if your prescription drug contains an MAOI, ask a doctor or pharmacist before taking this product.

Ask a doctor before use if you have
• heart disease • high blood pressure • thyroid disease • diabetes • trouble urinating due to an enlarged prostate gland • cough that occurs with too much phlegm (mucus) • cough that lasts or is chronic such as occurs with smoking, asthma, chronic bronchitis or emphysema

Ask a doctor or pharmacist before use if you are taking any other oral nasal decongestant or stimulant.

When using this product do not use more than directed.

Stop use and ask a doctor if
• you get nervous, dizzy, or sleepless
• symptoms do not get better within 7 days or are accompanied by fever
• cough lasts more than 7 days, comes back, or is accompanied by fever, rash, or persistent headache. These could be signs of a serious condition.

If pregnant or breast-feeding, ask a health professional before use.

Keep out of reach of children. In case of overdose, get medical help or contact a Poison Control Center right away.

Directions

• do not take more than 4 doses in any 24-hour period.

AGE | DOSE
Adults and children 12 years of age and over | Take 2 teaspoonfuls (10 mL) every 6 hours
Children under 12 years of age | do not use

Other information

• Tamper Evident Feature: Do not use if inner seal is torn, cut, or opened
• Store at controlled room temperature 15°- 30°C (59° - 86°F)
• Avoid excessive heat or humidity.

Inactive ingredients

Citric Acid, Flavor, Methylparaben, Potassium Citrate, Propylene Glycol, Propylparaben, Purified Water, Sorbitol, Sucralose

Questions or comments?

call weekdays from 8AM to 4PM AST at 1.787.608.0882

NEW FORMULA

Contains the same active ingredients as Tusnel®*

SUGAR FREE
DYE FREE
ALCOHOL FREE
SACCHARIN FREE

COMMITTED TO HEALTH AND WELL-BEING
WWW.ACTIPHARMA.NET

Manufactured in USA with imported ingredients for ActiPharma, Inc.
San Juan, PR 00917.

* Tusnel® is a registered trademark of Llorens Pharmaceutical Corp. This product is not manufactured, distributed or marketed by Llorens Pharmaceutical Corp.